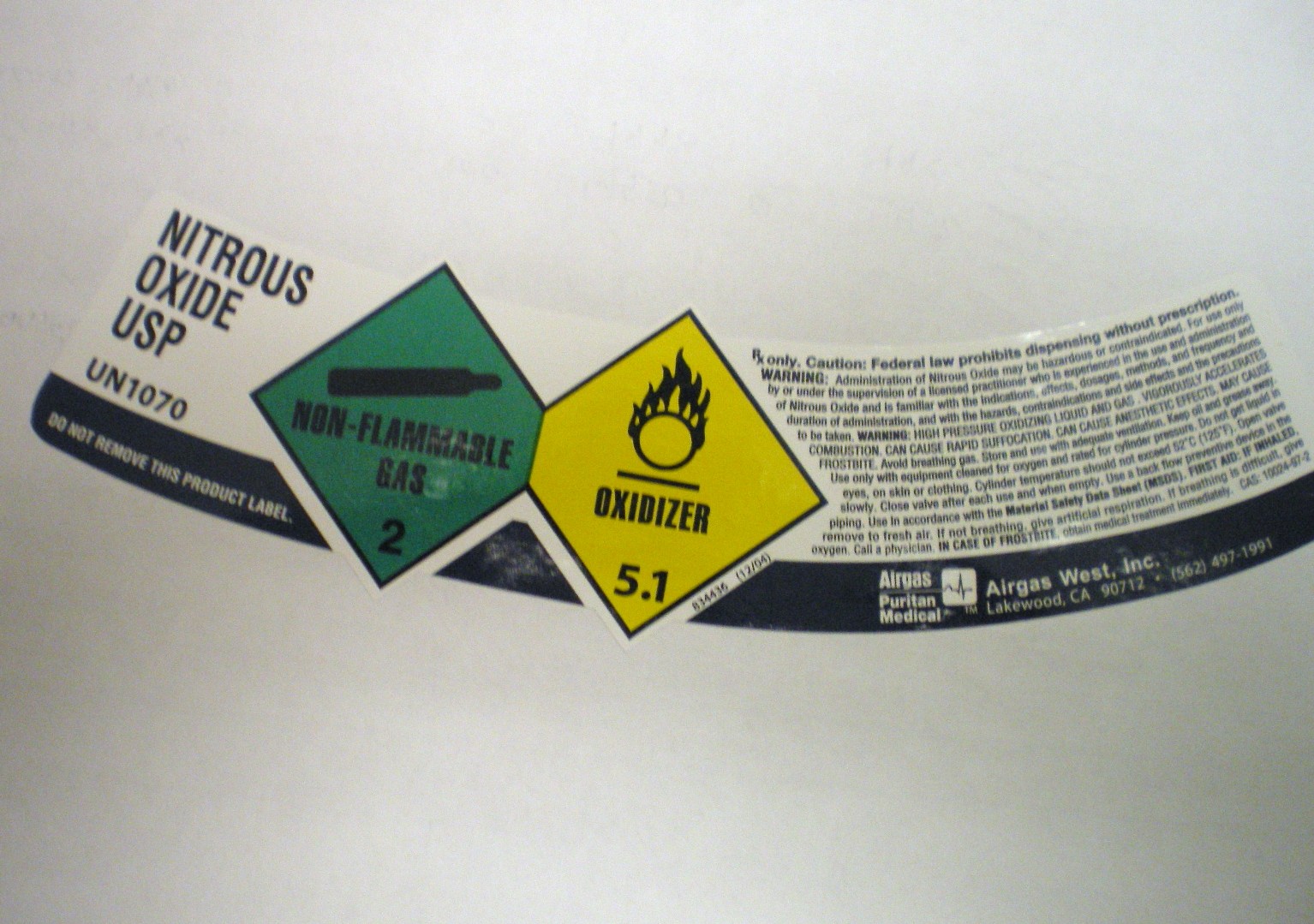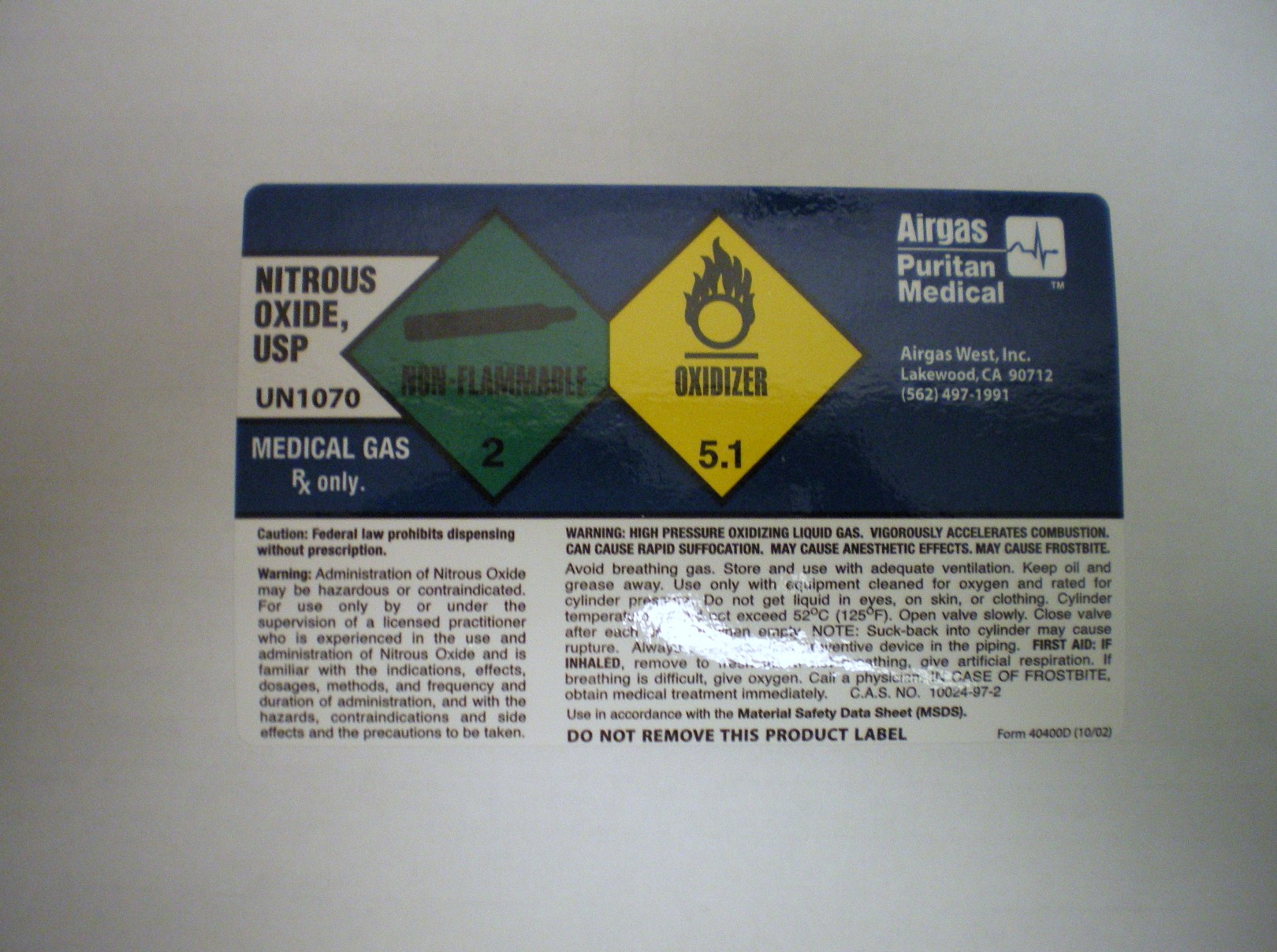 DRUG LABEL: Nitrous Oxide
NDC: 10678-006 | Form: GAS
Manufacturer: Airgas-West, Inc.
Category: prescription | Type: HUMAN PRESCRIPTION DRUG LABEL
Date: 20100525

ACTIVE INGREDIENTS: Nitrous Oxide 992 mL/1 L

nitrous oxide

PACKAGE LABEL

NITROUS OXIDE, USP
UN1070
DO NOT REMOVE THIS PRODUCT LABEL
Non-Flammable Gas 2 OXIDIZER 5.1
834436 (12/04)
Rx Only. CAUTION: Federal law prohibits dispensing without a prescription.
WARNING: Administration of Nitrous Oxide may be hazardous or contraindicated. For use by or under the supervision of a licensed practitioner who is experienced in the use and administration of Nitrous Oxide and is familiar with the indications, effects, dosages, methods, and frequency and duration of administration, and with the hazards, contraindications and side effects, and the precautions to be taken.
WARNING: HIGH PRESSURE OXIDIZING LIQUID AND GAS. VIGOROUSLY ACCELERATES COMBUSTION. CAN CAUSE RAPID SUFFOCATION. CAN CAUSE ANESTHETIC EFFECTS. MAY CAUSE FROSTBITE. Avoid breathing gas. Store and use with adequate ventilation. Keep oil and grease away. Use only with equipment cleaned for oxygen and rated for cylinder pressure. Do not get liquid in eyes, on skin or clothing. Cylinder temperature should not exceed 52oC(125oF). Open valve slowly. Close valve after each use and when empty. Use a back flow preventive device in the piping. Use in accordance with the Material Safety Data Sheet (MSDS).
FIRST AID: IF INHALED, remove to fresh air. If not breathing, give artificial respiration. If breathing is difficult, give oxygen. Call a physician. IN CASE OF FROSTBITE, obtain medical treatment immediately. CAS: 10024-97-2
AIRGAS PURITAN MEDICAL Distributed By: Airgas West, Inc. Lakewood, CA 90712 (562) 497-1991

PACKAGE LABEL

NITROUS OXIDE, USP
UN1070
MEDICAL GAS Rx only.
NON-FLAMMABLE 2 OXIDIZER 5.1
AIRGAS PURITAN MEDICAL Distributed By: Airgas West, Inc. Lakewood, CA 90712 (562) 497-1991
CAUTION: Federal law prohibits dispensing without a prescription.
WARNING: Administration of Nitrous Oxide may be hazardous or contraindicated. For use by or under the supervision of a licensed practitioner who is experienced in the use and administration of Nitrous Oxide and is familiar with the indications, effects, dosages, methods, and frequency and duration of administration, and with the hazards, contraindications and side effects, and the precautions to be taken.
WARNING: HIGH PRESSURE OXIDIZING LIQUID GAS. VIGOROUSLY ACCELERATES COMBUSTION. CAN CAUSE RAPID SUFFOCATION. MAY CAUSE ANESTHETIC EFFECTS. MAY CAUSE FROSTBITE. Avoid breathing gas. Store and use with adequate ventilation. Keep oil and grease away. Use only with equipment cleaned for oxygen and rated for cylinder pressure. Do not get liquid in eyes, on skin or clothing. Cylinder temperature should not exceed 52oC(125oF). Open valve slowly. Close valve after each use and when empty. NOTE: Suck-back into cylinder may cause rupture. Always use a back flow preventive device in the piping.
FIRST AID: IF INHALED, remove to fresh air. If not breathing, give artificial respiration. If breathing is difficult, give oxygen. Call a physician. IN CASE OF FROSTBITE, obtain medical treatment immediately. CAS: 10024-97-2
Use in accordance with the Material Safety Data Sheet (MSDS). DO NOT REMOVE THIS PRODUCT LABEL.
Form 40400D (10/02)